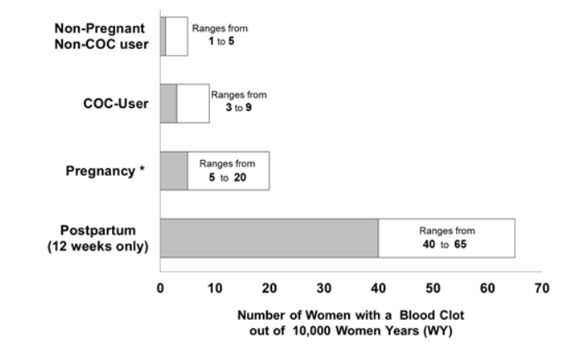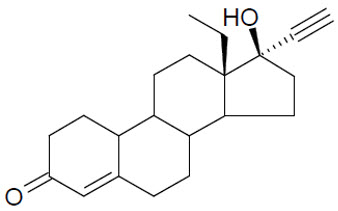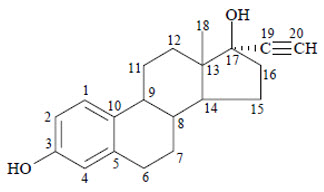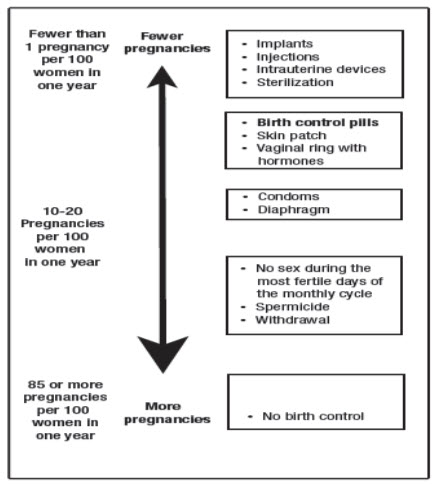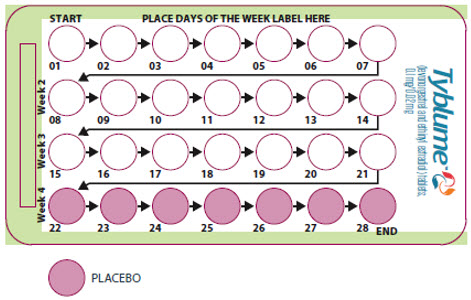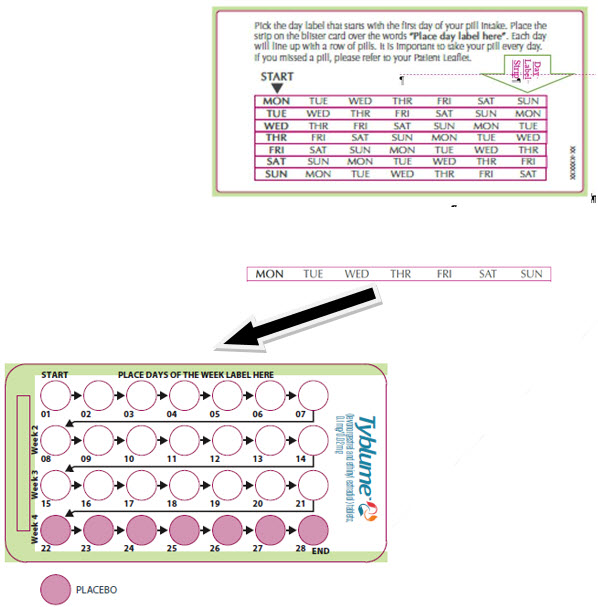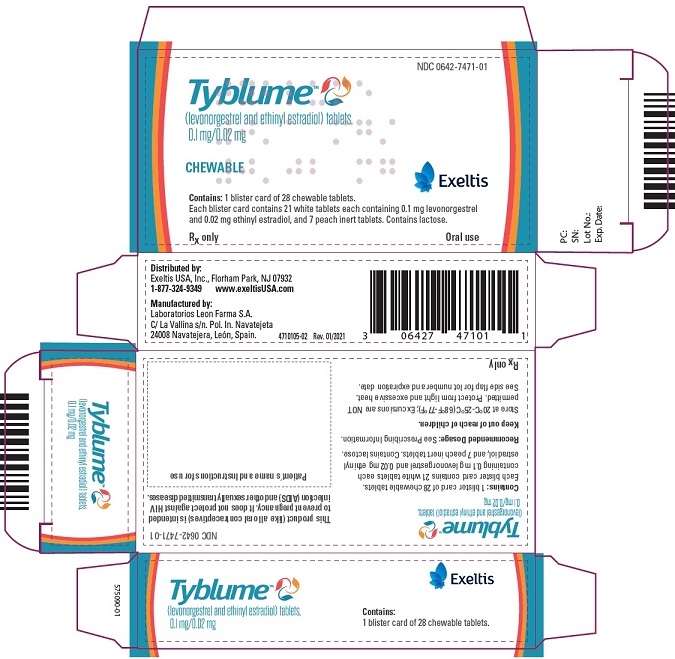 DRUG LABEL: Tyblume
NDC: 0642-7471 | Form: KIT | Route: ORAL
Manufacturer: Exeltis USA, Inc.
Category: prescription | Type: HUMAN PRESCRIPTION DRUG LABEL
Date: 20230212

ACTIVE INGREDIENTS: LEVONORGESTREL 0.1 mg/1 1; ETHINYL ESTRADIOL 0.02 mg/1 1
INACTIVE INGREDIENTS: LACTOSE MONOHYDRATE; STARCH, CORN; POVIDONE K30; CROSPOVIDONE; MAGNESIUM STEARATE; ANHYDROUS LACTOSE; STARCH, CORN; POVIDONE K30; CROSPOVIDONE; MAGNESIUM STEARATE

HIGHLIGHTS OF PRESCRIBING INFORMATION

These highlights do not include all the information needed to use TYBLUME safely and effectively. See full prescribing information for TYBLUME.
TYBLUME (levonorgestrel and ethinyl estradiol) tablets, for oral use
Initial U.S. Approval: 1968 (norgestrel and ethinyl estradiol)

WARNING: CIGARETTE SMOKING AND SERIOUS CARDIOVASCULAR EVENTS

See full prescribing information for complete boxed warning.

- TYBLUME is contraindicated in women over 35 years old who smoke. (4)
- Cigarette smoking increases the risk of serious cardiovascular side effects from combination hormonal contraceptive (CHC) use. (5.1)

1 INDICATIONS AND USAGE

TYBLUME (levonorgestrel and ethinyl estradiol tablets) is a combination of levonorgestrel, a progestin, and ethinyl estradiol, an estrogen, indicated for use by females of reproductive potential to prevent pregnancy. (1)

2 DOSAGE AND ADMINISTRATION

- Take TYBLUME in one of two ways: (1) swallow whole on an empty stomach or (2) chew and then immediately swallow with a full glass of 240 mL water on an empty stomach. (2.1)
  - Start on Day 1 and take each tablet at the same time every day in the order directed on the blister pack, or (2)
  - Start on a Sunday and take each tablet at the same time every day in the order directed on the blister pack. (2)
- Take one tablet daily for 28 consecutive days: one white active tablet daily during the first 21 consecutive days, followed by one peach inactive tablet daily during the 7 following days. (2)

3 DOSAGE FORMS AND STRENGTHS

A TYBLUME pack consists of 28 tablets:

- 21 white tablets (active), each containing levonorgestrel 0.1 mg and ethinyl estradiol 0.02 mg.
- 7 peach-colored tablets (inactive placebo).

4 CONTRAINDICATIONS

- High risk of arterial or venous thrombotic diseases. (4)
- Breast cancer or other estrogen- or progestin-sensitive cancer. (4)
- Liver tumors, acute viral hepatitis or decompensated cirrhosis. (4)
- Undiagnosed abnormal uterine bleeding. (4)
- Use of Hepatitis C drug combinations containing ombitasvir/paritaprevir/ritonavir, with or without dasabuvir. (4)

5 WARNINGS AND PRECAUTIONS

- Vascular risks: Stop if a thrombotic or thromboembolic event occurs. Stop TYBLUME at least 4 weeks before and through 2 weeks after major surgery. Start no earlier than 4 weeks after delivery, in females who are not breast-feeding. Consider cardiovascular risk factors before initiating in all females, particularly those over 35 years. (5.1, 5.4)
- Liver disease: Discontinue TYBLUME if jaundice occurs. (5.2)
- Hypertension: If used in females with well-controlled hypertension, monitor blood pressure. Stop use of TYBLUME if blood pressure rises significantly. (5.3)
- Gallbladder disease: May cause or worsen gallbladder disease. (5.5)
- Adverse carbohydrate and lipid effect: Monitor glucose in prediabetic and diabetic females using TYBLUME. Consider an alternate contraceptive method for females with uncontrolled dyslipidemia. (5.6)
- Headache: Evaluate significant change in headaches and discontinue TYBLUME if indicated. (5.7)
- Uterine bleeding: May cause irregular bleeding or amenorrhea. Evaluate for other causes if symptoms persist. (5.8)

6 ADVERSE REACTIONS

Common adverse reactions are: headache, abdominal pain, nausea, metrorrhagia, vaginal moniliasis and pain, acne, and vaginitis. (6)

To report SUSPECTED ADVERSE REACTIONS, contact Exeltis USA, Inc. at 1-877-324-9349 or FDA at 1-800-FDA-1088 or www.fda.gov/medwatch.

7 DRUG INTERACTIONS

Enzyme inducers (e.g., CYP3A4): May decrease the effectiveness of TYBLUME or increase breakthrough bleeding. Counsel patients to use a back-up or alternative method of contraception when enzyme inducers are used with TYBLUME. (7.1, 7.2)

8 USE IN SPECIFIC POPULATIONS

- Lactation: Advise use of another method; TYBLUME can decrease milk production. (8.2)

FULL PRESCRIBING INFORMATION

WARNING: CIGARETTE SMOKING AND SERIOUS CARDIOVASCULAR EVENTS

Cigarette smoking increases the risk of serious cardiovascular events from combined hormonal contraceptive (CHC) use. This risk increases with age, particularly in women over 35 years of age, and with the number of cigarettes smoked. For this reason, CHCs, including TYBLUME (levonorgestrel and ethinyl estradiol) tablets, are contraindicated in women who are over 35 years of age and smoke [ see Contraindications (4) and Warnings and Precautions (5.1)].

1 INDICATIONS AND USAGE

TYBLUME is indicated for use by females of reproductive potential to prevent pregnancy.

2 DOSAGE AND ADMINISTRATION

2.1 Important Administration Instructions

Take TYBLUME in one of two ways: (1) swallow whole on an empty stomach or (2) chew and then immediately swallow with a full glass of 240 mL of water on an empty stomach [see Dosage and Administration (2.2)].

2.2 Additional Administration Information

To achieve maximum contraceptive effectiveness, take TYBLUME exactly as directed (one tablet orally at the same time every day) and at intervals not exceeding 24 hours. The failure rate may increase when tablets are missed or taken incorrectly. The recommended dosage of TYBLUME is one tablet daily for 28 consecutive days: one white active tablet daily during the first 21 consecutive days, followed by one peach inactive tablet daily during the 7 following days (see Table 1).

Table 1 Instructions for Administration of TYBLUME
Starting TYBLUME in females with no current use of hormonal contraception (start on Day 1 or Sunday)
Day 1 start
- Take first tablet without food (i.e. empty stomach) on the first day of menses
- Take subsequent tablets once daily at the same time each day
- Begin each subsequent 28-day pack on the same day of the week as the first cycle pack (i.e., on the day after taking the last tablet)
Sunday start
- Take first tablet without food (i.e. empty stomach) on the first Sunday after the onset of menstrual period
- Take subsequent tablets once daily at the same time each day
- Use additional nonhormonal contraception for the first seven days of TYBLUME use
- Begin each subsequent 28-day pack on the same day of the week as the first cycle pack (i.e., on the day after taking the last tablet)
Switching to TYBLUME from another contraceptive method
 | Start TYBLUME:
- A combined oral contraceptive (COC) | - On the day when the new pack of the previous COC would have been started
- Transdermal system | - On the day when next application would have been scheduled
- Vaginal ring | - On the day when next insertion would have been scheduled
- Injection | - On the day when next injection would have been scheduled
- Intrauterine system | - On the day of removal
- Implant | - On the day of removal
Complete instructions to facilitate patient counseling on proper tablet usage are located in the FDA-Approved Patient Labeling (Instructions for Use).

2.3 Missed Doses

Instruct patients about the handling of missed doses (e.g., to take a missed tablet as soon as possible) and to follow the dosing instructions provided in the FDA-approved patient labeling (Instructions for Use).

Table 2 Instructions for Missed TYBLUME
- If one white active tablet is missed in Weeks 1, 2, or 3 | Take the missed active tablet as soon as possible, even if two active tablets are taken in one day. Continue taking one tablet a day until the pack is finished.
- If two white active tablets are missed in Week 1 or Week 2 | Take two active tablets as soon as possible. Then, take two active tablets the next day. This means taking 4 tablets in 2 days. Continue taking one tablet a day until the pack is finished. Additional nonhormonal contraception (such as condoms and spermicide) should be used as back-up if the patient has sex within 7 days after missing tablets.
- If two white active tablets are missed in the third week or three or more active tablets are missed in a row in Weeks 1, 2, or 3 | Day 1 start: Throw out the rest of the 28-day pack and start a new pack that same day. Sunday start: Continue taking one tablet a day until Sunday, then throw out the rest of the pack and start a new pack that same day. Additional nonhormonal contraception (such as condoms and spermicide) should be used as back-up if the patient has sex within 7 days after missing tablets.
- If one or more peach (inactive) tablets are missed in the fourth week | Throw away the missed inactive tablets. Keep taking one tablet each day until the pack is empty. Back-up nonhormonal birth-control method is not needed but take the next pack on time.

2.4 Administration Recommendations after Vomiting or Acute Diarrhea

If vomiting or acute diarrhea occurs within 3 to 4 hours after taking an active tablet, take the new active tablet (scheduled for the next day) as soon as possible. If more than two active tablets are missed, see the recommendations in Table 2 [see Dosage and Administration (2.3)].

3 DOSAGE FORMS AND STRENGTHS

One pack of TYBLUME consists of 28 tablets:

- 21 active tablets are white, round, and debossed with 30 on one side and L2 on the other side. Each active tablet contains levonorgestrel 0.1 mg and ethinyl estradiol 0.02 mg.
- 7 inactive tablets (placebo) are peach-colored, round, and debossed with 1 on one side and L2 on the other side.

4 CONTRAINDICATIONS

TYBLUME is contraindicated in females who are known to have the following conditions:

- A high risk of arterial or venous thrombotic diseases. Examples include females who are known to:
  - Smoke, if over age 35 [see Boxed Warning and Warnings and Precautions (5.1)]
  - Have current or history of deep vein thrombosis or pulmonary embolism [see Warnings and Precautions (5.1)]
  - Have cerebrovascular disease [see Warnings and Precautions (5.1)]
  - Have coronary artery disease [see Warnings and Precautions (5.1)]
  - Have thrombogenic valvular or thrombogenic rhythm diseases of the heart (for example, subacute bacterial endocarditis with valvular disease, or atrial fibrillation) [see Warnings and Precautions (5.1)]
  - Have inherited or acquired hypercoagulopathies [see Warnings and Precautions (5.1)]
  - Have uncontrolled hypertension or hypertension with vascular disease [see Warnings and Precautions (5.3)]
  - Have diabetes mellitus and are over age 35, diabetes mellitus with hypertension or vascular disease or other end-organ damage, or diabetes mellitus of > 20 years duration [see Warnings and Precautions (5.6)]
  - Have headaches with focal neurological symptoms, migraine headaches with aura, or over age 35 with any migraine headaches [see Warnings and Precautions (5.7)]
- Current or history of breast cancer or other estrogen- or progestin-sensitive cancer
- Liver tumors, acute viral hepatitis, or severe (decompensated) cirrhosis [see Warnings and Precautions (5.2)]
- Undiagnosed abnormal uterine bleeding [see Warnings and Precautions (5.8)]
- Use of hepatitis C drug combinations containing ombitasvir/paritaprevir/ritonavir, with or without dasabuvir, due to the potential for ALT elevations [see Warnings and Precautions (5.14)]

5 WARNINGS AND PRECAUTIONS

5.1 Thromboembolic Disorders and Other Vascular Problems

Before starting TYBLUME evaluate any past medical history or family history of thrombotic or thromboembolic disorders and consider whether the history suggests an inherited or acquired hypercoagulopathy. TYBLUME is contraindicated in females with a high risk of arterial or venous thrombotic/thromboembolic diseases [see Contraindications (4)].

- Stop TYBLUME if an arterial or venous thrombotic/thromboembolic event occurs.
- Stop TYBLUME if there is unexplained loss of vision, proptosis, diplopia, papilledema, or retinal vascular lesions and evaluate for retinal vein thrombosis immediately.
- Discontinue TYBLUME during prolonged immobilization. If feasible, stop TYBLUME at least four weeks before and through two weeks after major surgery, or other surgeries known to have an elevated risk of thromboembolism.
- Start TYBLUME no earlier than four weeks after delivery in females who are not breastfeeding. The risk of postpartum thromboembolism decreases after the third postpartum week, whereas the likelihood of ovulation increases after the third postpartum week.

Arterial Events

CHCs increase the risk of cardiovascular events and cerebrovascular events, such as myocardial infarction and stroke. The risk is greater among older women (> 35 years of age), smokers, and females with hypertension, dyslipidemia, diabetes, or obesity.

TYBLUME is contraindicated in women over 35 years of age who smoke [see Contraindications (4)] . Cigarette smoking increases the risk of serious cardiovascular events from CHC use. This risk increases with age, particularly in women over 35 years of age, and with the number of cigarettes smoked.

Venous Events

Use of CHCs increases the risk of venous thromboembolic events (VTEs), such as deep vein thrombosis and pulmonary embolism. Risk factors for VTEs include smoking, obesity, and family history of VTE, in addition to other factors that contraindicate use of CHCs [see Contraindications (4)] . While the increased risk of VTE associated with use of CHCs is well-established, the rates of VTE are even greater during pregnancy, and especially during the postpartum period (see Figure 1). The rate of VTE in females using COCs has been estimated to be 3 to 9 cases per 10,000 woman-years.

The risk of VTE is highest during the first year of use of a CHC and when restarting hormonal contraception after a break of four weeks or longer. Based on results from a few studies, there is some evidence that this is true for non-oral products as well. The risk of thromboembolic disease due to CHCs gradually disappears after CHC use is discontinued.

Figure 1 shows the risk of developing a VTE for females who are not pregnant and do not use oral contraceptives, for females who use oral contraceptives, for pregnant females, and for females in the postpartum period. To put the risk of developing a VTE into perspective: If 10,000 females who are not pregnant and do not use oral contraceptives are followed for one year, between 1 and 5 of these females will develop a VTE.

Figure 1 Likelihood of Developing a VTE

*Pregnancy data based on actual duration of pregnancy in the reference studies. Based on a model assumption that pregnancy duration is nine months, the rate is 7 to 27 per 10,000 WY.

5.2 Liver Disease

Elevated Liver Enzymes

TYBLUME is contraindicated in females with acute viral hepatitis or severe (decompensated) cirrhosis of the liver [see Contraindications (4)]. Discontinue TYBLUME if jaundice develops. Acute liver test abnormalities may necessitate the discontinuation of CHC use until the liver tests return to normal and CHC causation has been excluded.

Liver Tumors

TYBLUME is contraindicated in females with benign or malignant liver tumors [see Contraindications (4)] . CHCs increase the risk of hepatic adenomas. An estimate of the attributable risk is 3.3 cases/100,000 CHC users. Rupture of hepatic adenomas may cause death from abdominal hemorrhage.

Studies have shown an increased risk of developing hepatocellular carcinoma in long-term (> 8 years) CHC users. The attributable risk of liver cancers in CHC users is less than one case per million users.

5.3 Hypertension

TYBLUME is contraindicated in females with uncontrolled hypertension or hypertension with vascular disease [see Contraindications (4)] . For all females, including those with well-controlled hypertension, monitor blood pressure at routine visits and stop TYBLUME if blood pressure rises significantly.

An increase in blood pressure has been reported in females using CHCs, and this increase is more likely in older women with extended duration of use. The effect of CHCs on blood pressure may vary according to the progestin in the CHC.

5.4 Age-related Considerations

The risk for cardiovascular disease and prevalence of risk factors for cardiovascular disease increase with age. Certain conditions, such as smoking and migraine headache without aura, that do not contraindicate CHC use in younger females, are contraindications to use in women over 35 years of age [see Contraindications (4) and Warnings and Precautions (5.1)]. Consider the presence of underlying risk factors that may increase the risk of cardiovascular disease or VTE, particularly before initiating a CHC for women over 35 years, such as:

- Hypertension
- Diabetes
- Dyslipidemia
- Obesity

5.5 Gallbladder Disease

Studies suggest an increased risk of developing gallbladder disease among CHC users. Use of CHCs may also worsen existing gallbladder disease.

A past history of CHC-related cholestasis predicts an increased risk with subsequent CHC use. Females with a history of pregnancy-related cholestasis may be at an increased risk for CHC related cholestasis.

5.6 Adverse Carbohydrate and Lipid Metabolic Effects

Hyperglycemia

TYBLUME is contraindicated in diabetic women over age 35, or females who have diabetes with hypertension, nephropathy, retinopathy, neuropathy, other vascular disease, or females with diabetes of > 20 years duration [see Contraindications (4)]. TYBLUME may decrease glucose tolerance. Carefully monitor prediabetic and diabetic females who are using TYBLUME.

Dyslipidemia

Consider alternative contraception for females with uncontrolled dyslipidemia. TYBLUME may cause adverse lipid changes.

Females with hypertriglyceridemia, or a family history thereof, may have an increase in serum triglyceride concentrations when using TYBLUME, which may increase the risk of pancreatitis.

5.7 Headache

TYBLUME is contraindicated in females who have headaches with focal neurological symptoms or have migraine headaches with aura, and in women over age 35 years who have migraine headaches with or without aura [see Contraindications (4)].

If a woman using TYBLUME develops new headaches that are recurrent, persistent, or severe, evaluate the cause and discontinue TYBLUME if indicated. Consider discontinuation of TYBLUME if there is an increased frequency or severity of migraines during CHC use (which may be prodromal of a cerebrovascular event).

5.8 Bleeding Irregularities and Amenorrhea

Unscheduled Bleeding and Spotting

Females using TYBLUME may experience unscheduled (breakthrough or intracyclic) bleeding and spotting, especially during the first three months of use. Bleeding irregularities may resolve over time or by changing to a different contraceptive product. If bleeding persists or occurs after previously regular cycles, evaluate for causes such as pregnancy or malignancy.

Amenorrhea and Oligomenorrhea

Females who use TYBLUME may experience absence of scheduled (withdrawal) bleeding, even if they are not pregnant.

If scheduled bleeding does not occur, consider the possibility of pregnancy. If the patient has not adhered to the prescribed dosing schedule (missed one or two active tablets or started taking them on a day later than she should have), consider the possibility of pregnancy at the time of the first missed period and perform appropriate diagnostic measures. If the patient has adhered to the prescribed dosing schedule and misses two consecutive periods, rule out pregnancy.

After discontinuation of a CHC, amenorrhea or oligomenorrhea may occur, especially if these conditions were pre-existent.

5.9 Depression

Carefully observe females with a history of depression and discontinue TYBLUME if depression recurs to a serious degree. Data on the association of CHCs with onset of depression or exacerbation of existing depression are limited.

5.10 Cervical Cancer

Some studies suggest that CHCs are associated with an increase in the risk of cervical cancer or intraepithelial neoplasia. There is controversy about the extent to which these findings are due to differences in sexual behavior and other factors.

5.11 Effect on Binding Globulins

The estrogen component of TYBLUME may raise the serum concentrations of thyroxine-binding globulin, sex hormone-binding globulin, and cortisol-binding globulin. The dose of replacement thyroid hormone or cortisol therapy may need to be increased.

5.12 Hereditary Angioedema

In females with hereditary angioedema, exogenous estrogens may induce or exacerbate symptoms of angioedema.

5.13 Chloasma

Chloasma may occur with TYBLUME use, especially in females with a history of chloasma gravidarum. Advise females with a history of chloasma to avoid exposure to the sun or ultraviolet radiation while using TYBLUME.

5.14 Risk of Liver Enzyme Elevations with Concomitant Hepatitis C Treatment

During clinical trials with the Hepatitis C combination drug regimen that contains ombitasvir/paritaprevir/ritonavir, with or without dasabuvir, ALT elevations greater than 5 times the upper limit of normal (ULN), including some cases greater than 20 times the ULN, were significantly more frequent in women using ethinyl estradiol-containing medications, such as COCs. COCs are contraindicated for use with Hepatitis C drug combinations containing ombitasvir/paritaprevir/ritonavir, with or without dasabuvir [see Contraindications (4)] . Discontinue TYBLUME prior to starting therapy with the combination drug regimen ombitasvir/paritaprevir/ritonavir, with or without dasabuvir.

TYBLUME can be restarted approximately 2 weeks following completion of treatment with the Hepatitis C combination drug regimen.

6 ADVERSE REACTIONS

The following serious adverse reactions with the use of CHCs are discussed elsewhere in labeling:

- Serious cardiovascular events [see Boxed Warning and Warnings and Precautions (5.1 and 5.4)]
- Vascular events [see Warnings and Precautions (5.1)]
- Liver disease [see Warnings and Precautions (5.2)]
- Hypertension [see Warnings and Precautions (5.3)]
- Gallbladder disease [see Warnings and Precautions (5.5)]
- Adverse carbohydrate and lipid metabolic effects [see Warnings and Precautions (5.6)]
- Headache [see Warnings and Precautions (5.7)]
- Bleeding irregularities and amenorrhea [see Warnings and Precautions (5.8)]
- Depression [see Warnings and Precautions (5.9)]
- Cervical cancer [see Warnings and Precautions (5.10)]
- Effect on binding globulins [see Warnings and Precautions (5.11)]
- Hereditary angioedema [see Warnings and Precautions (5.12)]
- Chloasma [see Warnings and Precautions (5.13)]
- Risk of liver enzyme elevations with concomitant hepatitis C treatment [see Warnings and Precautions (5.14)]

The following adverse reactions associated with the use of oral CHCs were identified in clinical studies or postmarketing reports. Because some of these reactions were reported voluntarily from a population of uncertain size, it is not always possible to reliably estimate their frequency or establish a causal relationship to drug exposure.

Common adverse reactions associated with oral CHCs are headache, abdominal pain, nausea, metrorrhagia, vaginal moniliasis and pain, acne, and vaginitis.

Additional adverse reactions that have been reported include the following:

Eye disorder: intolerance to contact lenses, steepening of corneal curvature

Gastrointestinal disorders: Abdominal bloating, vomiting

General disorders and administration site condition: Edema, fluid retention

Hepatobiliary disorders: Cholestatic jaundice

Psychiatric disorders: Change in libido, mood changes

Reproductive system and breast disorders: Amenorrhea, breast tenderness, breast pain, breast enlargement, increased cervical mucous, change in menstrual flow, unscheduled bleeding

Skin and subcutaneous tissue disorders: Acne, melasma [see Warnings and Precautions (5.13)]

Vascular disorders: Budd-Chiari syndrome, aggravation of varicose veins

7 DRUG INTERACTIONS

The sections below provide information on substances for which data on drug interactions with CHCs are available. There is little information available about the clinical effect of most drug interactions that may affect CHCs. However, based on the known pharmacokinetic effects of these drugs, clinical strategies to minimize any potential adverse effect on contraceptive effectiveness or safety are suggested.

Consult the approved product labeling of all concurrently used drugs to obtain further information about interactions with CHCs or the potential for metabolic enzyme or transporter system alterations.

No drug-drug interaction studies were conducted with TYBLUME.

7.1 Effects of Other Drugs on Combined Hormonal Contraceptives

Substances decreasing the Plasma Concentration of CHCs and Potentially Diminishing the Efficacy of CHCs

Table 3 Significant Drug Interactions Involving Substances That Affect CHCs
Metabolic Enzyme Inducers
Clinical effect | - Concomitant use of CHCs with metabolic enzyme inducers may decrease the plasma concentrations of the estrogen and/or progestin component of CHCs [see Clinical Pharmacology (12.3)] . - Decreased exposure of the estrogen and/or progestin component of CHCs may potentially diminish the effectiveness of CHCs and may lead to contraceptive failure or an increase in breakthrough bleeding.
Prevention or management | - Counsel females to use an alternative method of contraception or a backup method when enzyme inducers are used with CHCs. - Continue backup contraception for 28 days after discontinuing the enzyme inducer to maintain contraceptive reliability.
Examples | Aprepitant, barbiturates, bosentan, carbamazepine, efavirenz, felbamate, griseofulvin, oxcarbazepine, phenytoin, rifampin, primidone, phenylbutazone, rifabutin, rufinamide, topiramate, products containing St. John's wort, and certain protease inhibitors (see separate section on protease inhibitors below).
Colesevelam
Clinical effect | - Concomitant use of CHCs with colesevelam significantly decreases systemic exposure of ethinyl estradiol [see Clinical Pharmacology (12.3)]. - Decreased exposure of the estrogen component of CHCs may potentially reduce contraceptive efficacy or result in an increase in breakthrough bleeding, depending on the strength of ethinyl estradiol in the CHC.
Prevention or management | Administer 4 or more hours apart to attenuate this drug interaction.
a Induction potency of St. John's wort may vary widely based on preparation.

Substances increasing the systemic exposure of CHCs:

Co-administration of atorvastatin or rosuvastatin and CHCs containing ethinyl estradiol increase systemic exposure of ethinyl estradiol by approximately 20 to 25 percent. Ascorbic acid and acetaminophen may increase systemic exposure of ethinyl estradiol, possibly by inhibition of conjugation. CYP3A inhibitors such as itraconazole, voriconazole, fluconazole, grapefruit juice [The effect of grapefruit juice on CYP3A4 enzymes (e.g., strong vs. moderate inhibition) depends on its brand, concentration, and preparation.] , or ketoconazole may increase systemic exposure of the estrogen and/or progestin component of CHCs.

Human immunodeficiency virus (HIV)/hepatitis C virus (HCV) protease inhibitors and non-nucleoside reverse transcriptase inhibitors:

Significant decreases in systemic exposure of the estrogen and/or progestin have been noted when CHCs are co-administered with some HIV protease inhibitors (e.g., nelfinavir, ritonavir, darunavir/ritonavir, (fos)amprenavir/ritonavir, lopinavir/ritonavir, and tipranavir/ritonavir), some HCV protease inhibitors (e.g., boceprevir and telaprevir), and some non-nucleoside reverse transcriptase inhibitors (e.g., nevirapine).

In contrast, significant increases in systemic exposure of the estrogen and/or progestin have been noted when CHCs are co-administered with certain other HIV protease inhibitors (e.g., indinavir and atazanavir/ritonavir) and with other non-nucleoside reverse transcriptase inhibitors (e.g., etravirine).

7.2 Effects of Combined Hormonal Contraceptives on Other Drugs

Table 4 provides significant drug interaction information for drugs co-administered with TYBLUME.

Table 4 Significant Drug Interaction Information for Drugs Co-Administered with CHCs
Lamotrigine
Clinical effect | - Concomitant use of CHCs with lamotrigine may significantly decrease systemic exposure of lamotrigine due to induction of lamotrigine glucuronidation [see Clinical Pharmacology (12.3)]. - Decreased systemic exposure of lamotrigine may reduce seizure control.
Prevention or management | Dose adjustment may be necessary. Consult the approved product labeling for lamotrigine.
Thyroid Hormone Replacement Therapy or Corticosteroid Replacement Therapy
Clinical effect | Concomitant use of CHCs with thyroid hormone replacement therapy or corticosteroid replacement therapy may increase systemic exposure of thyroid-binding and cortisol-binding globulin [see Warnings and Precautions (5.11)].
Prevention or management | The dose of replacement thyroid hormone or cortisol therapy may need to be increased. Consult the approved product labeling for the therapy in use. [See Warnings and Precautions (5.11)].
Other Drugs
Clinical effect | Concomitant use of CHCs may decrease systemic exposure of acetaminophen, morphine, salicylic acid, and temazepam. Concomitant use with ethinyl estradiol-containing CHCs may increase systemic exposure of other drugs (e.g., cyclosporine, prednisolone, theophylline, tizanidine, and voriconazole).
Prevention or management | The dosage of drugs that can be affected by this interaction may need to be increased. Consult the approved product labeling for the concomitantly used drug.

7.3 Effect on Laboratory Tests

The use of CHCs may influence the results of certain laboratory tests, such as coagulation factors, lipids, glucose tolerance, and binding proteins.

7.4 Concomitant Use with HCV Combination Therapy – Liver Enzyme Elevation

CHCs are contraindicated for use with Hepatitis C drug combinations containing ombitasvir/paritaprevir/ritonavir, with or without dasabuvir [see Contraindications (4)]. Discontinue TYBLUME prior to starting therapy with the combination drug regimen ombitasvir/paritaprevir/ritonavir, with or without dasabuvir. TYBLUME can be restarted approximately 2 weeks following completion of treatment with the Hepatitis C combination drug regimen.

8 USE IN SPECIFIC POPULATIONS

8.1 Pregnancy

Risk Summary

There is no use for contraception in pregnancy; therefore, TYBLUME should be discontinued during pregnancy. Epidemiologic studies and meta-analyses have not found an increased risk of genital or nongenital birth defects (including cardiac anomalies and limb-reduction defects) following exposure to CHCs before conception or during early pregnancy.

In the U.S. general population, the estimated background risk of major birth defects and miscarriage in clinically recognized pregnancies is 2 to 4 percent and 15 to 20 percent, respectively.

8.2 Lactation

Risk Summary

Contraceptive hormones and/or metabolites are present in human milk. CHCs can reduce milk production in breast-feeding females. This reduction can occur at any time but is less likely to occur once breast-feeding is well established. When possible, advise the nursing female to use other methods of contraception until she discontinues breast-feeding [see Dosage and Administration (2.2)]. The developmental and health benefits of breast-feeding should be considered along with the mother's clinical need for TYBLUME and any potential adverse effects on the breast-fed child from TYBLUME or from the underlying maternal condition.

Data

Small amounts of oral-contraceptive steroids and/or metabolites have been identified in the milk of nursing mothers, and a few adverse effects on the child have been reported, including jaundice and breast enlargement. In addition, combination oral contraceptives given in the postpartum period may interfere with lactation by decreasing the quantity and quality of breast milk.

8.4 Pediatric Use

The safety and effectiveness of TYBLUME have been established in females of reproductive potential. Efficacy is expected to be the same for post-menarchal females under the age of 17 as for users 17 years and older. The use of TYBLUME before menarche is not indicated.

8.5 Geriatric Use

TYBLUME has not been studied in postmenopausal women and is not indicated in this population.

8.6 Hepatic Impairment

The pharmacokinetics of TYBLUME have not been studied in women with hepatic impairment. However, steroid hormones may be poorly metabolized in patients with hepatic impairment. Acute or chronic disturbances of liver function may necessitate the discontinuation of COC use until markers of liver function return to normal and COC causation has been excluded [see Contraindications (4) and Warnings and Precautions (5.2)] .

8.7 Body Mass Indexes

Data on differences in safety and effectiveness (if any) of TYBLUME between patients with high BMI and lower BMI are not available.

10 OVERDOSAGE

Overdose may cause nausea and uterine bleeding in females.

11 DESCRIPTION

TYBLUME (levonorgestrel and ethinyl estradiol) tablets is an oral contraceptive product. A TYBLUME pack consists of 21 white active tablets and 7 peach-colored inactive tablets.

The twenty-one white active tablets each contain 0.1 mg of levonorgestrel, a progestin, and 0.02 mg of ethinyl estradiol, an estrogen. Each tablet also contains the following inactive ingredients: corn starch, crospovidone, lactose monohydrate, magnesium stearate, povidone, and pregelatinized starch.

Seven peach-colored inactive tablets, each contains anhydrous lactose, corn starch, crospovidone, D&C yellow No. 10 aluminum lake, FD&C Red No. 40 aluminum lake, magnesium stearate, and povidone.

The chemical name for levonorgestrel is [18,19-Dinorpregn-4-en-20-yn-3-one, 13-ethyl-17-hydroxy-, (17α)-(-)-]. It has the molecular formula of C21H28O2, the molecular weight of 312.5, and the structural formula is provided below:

The chemical name for ethinyl estradiol is [19-norpregna-1,3,5(10)-trien-20-yne-3,17-diol, (17α)-]. It has the molecular formula of C20H24O2, the molecular weight of 296.4, and the structural formula is provided below:

12 CLINICAL PHARMACOLOGY

12.1 Mechanism of Action

CHCs lower the risk of becoming pregnant primarily by suppressing ovulation.

12.2 Pharmacodynamics

No specific pharmacodynamics studies were conducted with TYBLUME.

12.3 Pharmacokinetics

Absorption

No specific investigation of the absolute bioavailability of TYBLUME in humans has been conducted. However, literature indicates that levonorgestrel is rapidly and completely absorbed after oral administration (bioavailability about 100%) and is not subject to first-pass metabolism. Ethinyl estradiol is rapidly and almost completely absorbed from the gastrointestinal tract but, due to first-pass metabolism in gut mucosa and liver, the bioavailability of ethinyl estradiol is between 38% and 48%.

The kinetics of total levonorgestrel are non-linear due to an increase in binding of levonorgestrel to sex hormone binding globulin (SHBG), which is attributed to increased SHBG levels that are induced by the daily administration of ethinyl estradiol.

Table 5 provides a summary of pharmacokinetics of levonorgestrel and ethinyl estradiol after a single dose of TYBLUME in 32 female subjects only under fasting condition.

Table 5 Summary Mean (CV%) Pharmacokinetic Parameters from Single Dose Administration of TYBLUME
Analyte | Sample Size | Cmax (pg/mL) | Tmax (h) [Median (min – max)] | AUC0-T (pg*h/mL) | AUC0-∞ (pg*h/mL) | T1/2 (h)
EE | n = 32 | 53.22 (33.9) | 1.50 (1.00-2.25) | 477.75 (32.5) | 515.51 (31.0) | 16.42 (25.0)
LNG | n = 32 [n = 30 for AUC 0-∞ and T 1/2] | 3225.0 (33.1) | 0.75 (0.50-1.00) | 27586.0 (39.0) | 34099.0 (36.8) | 33.67 (31.8)

Distribution

Levonorgestrel in serum is primarily bound to SHBG. Ethinyl estradiol is about 97% bound to plasma albumin. Ethinyl estradiol does not bind to SHBG, but induces SHBG synthesis.

Elimination

Metabolism

Levonorgestrel: The most important metabolic pathway occurs in the reduction of the Δ4-3-oxo group and hydroxylation at positions 2α, 1β, and 16β, followed by conjugation. Most of the metabolites that circulate in the blood are sulfates of 3α,5β-tetrahydro-levonorgestrel, while excretion occurs predominantly in the form of glucuronides. Some of the parent levonorgestrel also circulates as 17β-sulfate. Metabolic clearance rates may differ among individuals by several-fold, and this may account in part for the wide variation observed in levonorgestrel concentrations among users.

Ethinyl estradiol: Cytochrome P450 enzymes (CYP3A4) in the liver are responsible for the 2-hydroxylation that is the major oxidative reaction. The 2-hydroxy metabolite is further transformed by methylation and glucuronidation prior to urinary and fecal excretion. Levels of Cytochrome P450 (CYP3A) vary widely among individuals and can explain the variation in rates of ethinyl estradiol 2-hydroxylation. Ethinyl estradiol is excreted in the urine and feces as glucuronide and sulfate conjugates, and undergoes enterohepatic circulation.

Excretion

The elimination half-life for levonorgestrel is approximately 36 ± 13 hours at steady state. Levonorgestrel and its metabolites are primarily excreted in the urine (40% to 68%) and about 16% to 48% are excreted in feces. The elimination half-life of ethinyl estradiol is 18 ± 4.7 hours at steady state.

13 NONCLINICAL TOXICOLOGY

13.1 Carcinogenesis, Mutagenesis, Impairment of Fertility

[see Warnings and Precautions (5.10)]

14 CLINICAL STUDIES

In a clinical trial with TYBLUME (levonorgestrel and ethinyl estradiol) tablets (0.1 mg and 0.02 mg, respectively), 1,477 subjects had 7,720 cycles of use and a total of 5 pregnancies were reported. This represented an overall pregnancy rate of 0.84 per 100 woman-years. These data included patients who did not take TYBLUME correctly. One or more tablets were missed during 1,479 (19%) of the 7,870 cycles; thus all tablets were taken during 6,391 (81%) of the 7,870 cycles. Of the total 7,870 cycles, a total of 150 cycles were excluded from the calculation of the Pearl Index due to the use of backup contraception and/or missing 3 or more consecutive tablets.

16 HOW SUPPLIED/STORAGE AND HANDLING

16.1 How Supplied

TYBLUME is available as follows:

Each blister card contains 28 tablets in the following order: 21 active tablets and 7 inactive tablets. The 21 active tablets are white, round, and debossed with 30 on one side and L2 on the other side; each contains levonorgestrel 0.1 mg and ethinyl estradiol 0.02 mg. The 7 inactive tablets (placebo) are peach-colored, round, and debossed with 1 on one side and L2 on the other
side.

- NDC 0642-7471-01, one carton containing 1 individual blister card

16.2 Storage and Handling

Store at controlled room temperature 20°C to 25°C (68°F to 77°F). Excursions are NOT permitted. Protect from light and excessive heat.

17 PATIENT COUNSELING INFORMATION

Advise the patient to read the FDA-approved patient labeling (Patient Information and Instructions for Use).

Cigarette Smoking

Advise women that cigarette smoking increases the risk of serious cardiovascular events from CHC use, and that women who are over 35 years old and smoke should not use TYBLUME [see Boxed Warning and Warning and Precautions (5.1)] .

Venous Thromboembolism

Advise women that the increased risk of VTE compared to non-users of CHCs is greatest after initially starting a CHC or restarting (following a 4-week or greater tablet-free interval) the same or a different CHC [see Warnings and Precautions (5.1)] .

Use During Pregnancy

Advise women that there is no reason to use TYBLUME during pregnancy. Instruct the woman to stop TYBLUME if pregnancy is confirmed during treatment [see Use in Specific Populations (8.1)].

Sexually Transmitted Infections

Advise women that TYBLUME does not protect against HIV-infection (AIDS) and other sexually transmitted infections.

Dosing, Administration and Missed Dose Instructions

Advise women to take TYBLUME in one of two ways: (1) swallow whole on an empty stomach or (2) chew and then immediately swallow with a full glass of 240 mL water on an empty stomach. Advise women to take one tablet daily by mouth at the same time every day [see Dosage and Administration (2.1)].

Advise women about what to do in the event tablets are missed. See "What should I do if I miss any TYBLUME tablets" section in FDA-approved patient labeling [see Dosage and Administration (2.3)].

Need for Additional Contraception

- Advise women to use a back-up or alternative method of contraception when enzyme inducers are used with TYBLUME [see Drug Interactions (7.1)] .
- Advise a woman who starts CHCs postpartum and has not yet had a period that she should use an additional method of contraception until she has taken a white tablet for 7 consecutive days.

Lactation

CHCs may reduce breast milk production; this is less likely to occur if breastfeeding is well established [see Use in Specific Populations (8.2)] .

Amenorrhea and Possible Symptoms of Pregnancy

Advise women that amenorrhea may occur. Advise women to contact their health care provider in the event of amenorrhea in two or more consecutive cycles or in case of symptoms of pregnancy such as morning sickness or unusual breast tenderness [see Warnings and Precautions (5.8)] .

Bleeding Irregularities

Advise women that irregular bleeding and/or spotting may occur. Bleeding irregularities typically resolve after the first few months of use. Advise women to consult their healthcare provider if bleeding irregularities persist for more than three to four months [see Warnings and Precautions (5.8)] .

Manufactured for: Exeltis USA, Inc., 180 Park Avenue, Suite 101, Florham Park, NJ 07932

Manufactured by: Laboratorios León Farma, S.A., León, Poligono Industrial Navatejera
C/ La Vallina, s/n 24008 Navatejera, Leon, Spain 24008

PATIENT INFORMATION
TYBLUME [tye bloom]
(levonorgestrel and ethinyl estradiol tablets) for oral use

What is the most important information I should know about TYBLUME (a type of birth control pill)?
Do not use TYBLUME if you smoke cigarettes and are over 35 years old. Smoking increases your risk of serious cardiovascular side effects (heart and blood vessel problems) from birth control, including death from heart attack, blood clots or stroke. This risk increases with age and the number of cigarettes you smoke.

What is TYBLUME?

- TYBLUME is a birth control pill (oral contraceptive) used by women to prevent pregnancy.
- TYBLUME does not protect against HIV infections (AIDS) and other sexually transmitted infections.

How does TYBLUME work for contraception?
Your chance of getting pregnant depends on how well you follow the directions for taking your birth control pills. The better you follow the directions, the less chance you have of getting pregnant.
Based on the results of one clinical study of a 28-day regimen of levonorgestrel 0.1mg/ethinyl estradiol 0.02 mg tablets, about 1 out of 100 women may get pregnant within the first year they use TYBLUME.
The following chart shows the chance of getting pregnant for women who use different methods of birth control. Each box on the chart contains a list of birth control methods that are similar in effectiveness. The most effective methods are at the top of the chart. The box on the bottom of the chart shows the chance of getting pregnant for women who do not use birth control and are trying to get pregnant.

Do not take TYBLUME if you:

- smoke and are over 35 years of age.
- have or have had blood clots in your arms, legs, lungs, or eyes.
- have a problem with your blood that makes it clot more than normal.
- have certain heart valve problems or an irregular heartbeat that increases your risk of having blood clots.
- had a stroke.
- had a heart attack.
- have high blood pressure that cannot be controlled by medicine or have high blood pressure with blood vessel problems.
- have diabetes and are over 35 years of age; have diabetes with high blood pressure, blood vessel problems, or kidney, eye, nerve, or blood vessel damage; or have had diabetes for more than 20 years.
- have certain kinds of severe migraine headaches with aura, numbness, weakness or changes in vision, or any migraine headaches if you are over 35 years of age.
- have liver problems, including liver tumors.
- have any unexplained vaginal bleeding.
- have or have had breast cancer or any cancer that is sensitive to female hormones.
- take any Hepatitis C drug combination containing ombitasvir/paritaprevir/ritonavir, with or without dasabuvir. This may increase levels of the liver enzyme "alanine aminotransferase" (ALT) in the blood.

If any of these conditions happen while you are taking TYBLUME, stop taking TYBLUME right away and talk to your healthcare provider. Use non-hormonal contraception when you stop taking TYBLUME.

Before you take TYBLUME, tell your healthcare provider about all of your medical conditions, including if you:

- are scheduled for surgery. TYBLUME may increase your risk of blood clots after surgery. You should stop taking TYBLUME at least 4 weeks before you have surgery and not restart TYBLUME until at least 2 weeks after your surgery.
- are pregnant or think you may be pregnant.
- are depressed now or have been depressed in the past.
- had yellowing of your skin or eyes (jaundice) caused by pregnancy (cholestasis of pregnancy).
- are breastfeeding or plan to breastfeed. TYBLUME may decrease the amount of breast milk you make. A small amount of the hormones in TYBLUME may pass into your breast milk. Talk to your healthcare provider about the best birth control method for you while breastfeeding.

Tell your healthcare provider about all the medicines you take, including prescription and over-the-counter medicines, vitamins and herbal supplements.
TYBLUME may affect the way other medicines work, and other medicines may affect how well TYBLUME works.
Women on thyroid replacement therapy or steroid therapy may need increased doses of thyroid hormone or steroid medicines.
Know the medicines you take. Keep a list of them to show your healthcare provider and pharmacist when you get a new medicine.

How should I take TYBLUME?

- Read the detailed Instructions for Use at the end of this Patient Information leaflet about the right way to take TYBLUME.
- Take TYBLUME exactly as your healthcare provider tells you to take it.
- You may take TYBLUME 1 of 2 ways:
  - Chew TYBLUME and then swallow TYBLUME with a full 8 oz (240 mL) glass of water right away , or
  - Swallow TYBLUME whole.
- Take TYBLUME on an empty stomach.

What are the possible side effects of TYBLUME?
TYBLUME may cause serious side effects, including:

- blood clots in your lungs, heart attack, or a stroke that may lead to death. Some other examples of serious blood clots include blood clots in the legs or eyes. Serious blood clots can happen especially if you smoke, are obese, or are older than 35 years of age. Serious blood clots are more likely to happen when you:
  - first start taking birth control pills.
  - restart the same or different birth control pills after not using them for a month or more.

Call your healthcare provider or go to the nearest emergency room right away if you have:

- leg pain that will not go away.
- sudden severe shortness of breath.
- sudden change in vision or blindness.
- chest pain.
- a sudden, severe headache unlike our usual headaches.
- weakness or numbness in your arm or leg.
- trouble speaking.

Other serious side effects include:

- liver problems, including:
  - jaundice. Call your healthcare provider if you have yellowing of your skin or eyes.
  - rare liver tumors.
- high blood pressure. You should see your healthcare provider to check your blood pressure regularly.
- gallbladder problems (cholestasis), especially if you previously had cholestasis of pregnancy.
- changes in the sugar and fat (cholesterol and triglycerides) levels in your blood.
- new or worsening headaches including migraine headaches.
- irregular or unusual vaginal bleeding and spotting between your menstrual periods, especially during the first 3 months of taking TYBLUME or the absence of menstrual periods (amenorrhea).
- depression.
- possible cancer in your cervix.
- swelling of your skin especially around your mouth, eyes, and in your throat (angioedema). Call your healthcare provider right away if you have a swollen face, lips, mouth, tongue or throat, which may lead to difficulty swallowing or breathing. Your chance of having angioedema is higher if you have a history of angioedema.
- dark patches of skin around your forehead, nose, cheeks and around your mouth, especially during pregnancy (chloasma). Women who tend to get chloasma should avoid spending a long time in sunlight, tanning booths, and under sun lamps while taking TYBLUME. Use sunscreen if you have to be in the sunlight.

The most common side effects of TYBLUME include:

- headache
- stomach (abdominal) pain
- nausea
- vaginal bleeding in between your periods

- vaginal yeast infection and pain
- acne
- infection or swelling of the vagina that can cause discharge, itching, and pain

These are not all the possible side effects of TYBLUME. For more information, ask your healthcare provider or pharmacist.
Call your doctor for medical advice about side effects. You may report side effects to FDA at 1-800-FDA-1088.

What else should I know about taking TYBLUME?

- If you are scheduled for any lab tests, tell your healthcare provider you are taking TYBLUME. Certain blood tests may be affected by TYBLUME.

How should I store TYBLUME?

- Store the blister card that TYBLUME comes in at room temperature between 68°F to 77°F (20°C to 25°C).
- Protect TYBLUME from light.
- Protect TYBLUME from high heat.

Keep TYBLUME and all medicines out of the reach of children.

General information about the safe and effective use of TYBLUME.
Medicines are sometimes prescribed for purposes other than those listed in Patient Information. Do not use TYBLUME for a condition for which it was not prescribed. Do not give TYBLUME to other people, even if they have the same symptoms that you have. It may harm them.
You can ask your pharmacist or healthcare provider for information about TYBLUME that is written for health professionals.
Manufactured for: Exeltis USA, Inc., Florham Park, NJ 07932
Manufactured by: Laboratorios León Farma, S.A., León, Spain

This Patient Information has been approved by the U.S. Food and Drug Administration.

Revised: May 2020

INSTRUCTIONS FOR USE TYBLUME [tye bloom] (levonorgestrel and ethinyl estradiol tablets) for oral use

Important information about taking TYBLUME (a type of birth control pill):

- Take 1 pill every day at the same time. Take the pills in the order directed on your blister pack.
- You may either chew 1 pill and then swallow it with a full 8oz (240mL) glass of water right away, or swallow the pill whole. Take the pill without food (on an empty stomach). Take the white pills and the peach pills the same way.
- Do not skip your pills, even if you do not have sex often. If you miss pills (including starting the pack late) you could get pregnant. The more pills you miss, the more likely you are to get pregnant.
- If you have trouble remembering to take TYBLUME, talk to your healthcare provider. When you first start taking TYBLUME, spotting or light bleeding in between your periods may occur. Contact your healthcare provider if this does not go away after a few months.
- You may feel sick to your stomach (nauseous), especially in the first few months after starting TYBLUME. If you feel sick to your stomach, do not stop taking TYBLUME. The nausea will usually go away. If your nausea does not go away, call your healthcare provider.
- Missing pills can also cause spotting or light bleeding in between your menstrual periods, even when you take the missed pills later. On the days you take 2 pills to make up for missed pills (see " What should I do if I miss any TYBLUME tablets?"), you could also feel sick to your stomach.
- Some women miss periods on hormonal birth control, even when they are not pregnant. However, if you miss a period and have not taken TYBLUME according to the directions, or miss 2 or more periods in a row, or feel like you may be pregnant, call your healthcare provider. If you have a positive pregnancy test, you should stop taking TYBLUME.
- If you have vomiting or diarrhea within 3 to 4 hours of taking your pill, take another pill of the same color (that was originally scheduled for you to take the next day) from your blister pack. If you miss more than 2 pills, see " What should I do if I miss any TYBLUME tablets?"
  - Continue to take all of your remaining pills in order. Start the first pill of your next blister pack the day after you finish your current blister pack. This will be 1 day earlier than originally scheduled. Continue on your new schedule.

Before you start taking TYBLUME:

- Decide what time of day you want to take your pill. It is important to take it at the same time every day and in the order as directed on your blister pack.
- Have non-hormonal backup birth control (such as condoms or spermicide) available and an extra full pack of pills as needed.

When should I start taking TYBLUME?

If you start taking TYBLUME and you have not used a hormonal birth control method before:

- There are 2 ways to start taking your birth control pills.
  - You can either start on a Sunday (Sunday Start) after you period starts, or
  - You can start on the first day (Day 1) of your natural menstrual period (Day 1 Start).

Your healthcare provider should tell you when to start taking your birth control pill.

If you use the Sunday Start, use a non-hormonal back-up birth control method such as condoms or spermicide for the first 7 days that you take TYBLUME. You do not need a back-up birth control method if you use the Day 1 Start.

If you start taking TYBLUME and you are switching from another birth control pill:

- Start your new TYBLUME pack on the same day that you would start the next pack of your previous birth control method.
- Do not continue taking the pills from your previous birth control pack.

If you start taking TYBLUME and previously used a vaginal ring or transdermal patch:

- Start using TYBLUME on the day you would have reapplied the next vaginal ring or transdermal patch.

If you start taking TYBLUME and you are switching from a progestin-only method such as an implant or injection:

- Start taking TYBLUME on the day of removal of your implant or on the day when you would have had your next injection.

If you start taking TYBLUME and you are switching from an intrauterine device or system (IUD or IUS):

- Start taking TYBLUME on the day of removal of your IUD or IUS.
- You do not need a back-up birth control method if your IUD or IUS is removed on the first day (Day 1) of your period. If your IUD or IUS is removed on any other day, use a non-hormonal back-up birth control method such as condoms or spermicide for the first 7 days that you take TYBLUME

If you start taking TYBLUME after you have given birth (postpartum) and have not yet had a menstrual period, use an additional method of birth control (such as condoms or spermicide) for the first 7 days that you take TYBLUME.

Keep a calendar to track your menstrual period:

If this is the first time you are taking birth control pills, read, "When should I start taking TYBLUME?" above. Follow these instructions for either a Sunday Start or a Day 1 Start.

Sunday Start:

You will use a Sunday Start if your healthcare provider told you to take your first pill on a Sunday. Use a non-hormonal back-up birth control method (such as condoms or spermicide) for the first 7 days of the first cycle that you take TYBLUME.

Instructions for using your pill pack:

- Look at your TYBLUME pack. See Figure A.
- Take pill 1 on the Sunday after your period starts.
- If your period starts on a Sunday, take pill "1" that day and see " Day 1 Start" instructions below.
- Take 1 pill every day in the order on the blister pack at the same time each day for 28 days.
- After taking the last pill on Day 28 from the blister pack, start taking the first pill from a new pack, on the same day of the week as the first pack (Sunday). Take the first pill in the new pack whether or not you are having your period.

Figure A

Day 1 Start:

You will use a Day 1 Start if your healthcare provider told you to take your first pill (Day 1) on the first day of your period.

- Take 1 pill every day in the order of the blister pack, at the same time each day, for 28 days.
- After taking the last pill on Day 28 from the blister pack, start taking the first pill from a new pack, on the same day of the week as the first pack. Take the first pill in the new pack whether or not you are having your period.

Instructions for using your pill pack:

Step 1.

Look at your TYBLUME pack. See Figure A.

The TYBLUME pack has:

- 21 white (active) tablets (pills) with hormones for Week 1 through Week 3
- 7 peach (inactive) tablets (pills) without hormones for Week 4

Step 2.

Find what day of the week you are to start taking your pills. If your period begins on a day other than Sunday, place the day label strip that starts with the first day of your period. For example, if your period begins on Monday, place the day label strip with Monday as the first day. See Figure B.

Figure B

Step 3.

Remove the white pill by pressing the pill through the foil in the bottom of the pill pack. Continue taking the white pills every day for 21 days.

Step 4.

On the first day of Week 4 start taking the peach pills. Take 1 peach pill every day for 7 days. Your period should start during this time.

Step 5.

When you have taken all of the peach pills in your pill pack, get a new pill pack and start taking the white pills.

- For a Day 1 start:
  Begin your next pill pack on the same day of the week as your first cycle pill pack.
- For a Sunday Start:
  Begin your next pill pack on Sunday.

What should I do if I miss any TYBLUME tablets?

If you miss 1 white pill in Weeks 1, 2, or 3 of your pill pack, follow these steps:

- Take it as soon as you remember. Take the next pill at your regular time. This means you may take 2 pills in 1 day.
- Then continue taking 1 pill every day until you finish the pack.
- You do not need to use a non-hormonal back-up birth control method if you have sex.

If you miss 2 white pills in Week 1 or Week 2 of your pill pack, follow these steps:

- Take 2 pills as soon as possible. Then, take 2 pills the next day. This means you will take 4 pills in 2 days.
- Then continue to take 1 pill every day until you finish the pack.
- Use a non-hormonal back-up birth control method (such as a condom or spermicide) if you have sex during the first 7 days after missing your pills.

If you miss 2 white pills in a row in Week 3, or you miss 3 or more white pills in a row during Weeks 1, 2, or 3 of your pill pack, follow these steps:

- If you are a Day 1 Starter:
  - Throw away the rest of the pill pack and start a new pack that same day.
- If you are a Sunday Starter:
  - Keep taking 1 white pill every day until Sunday. On Sunday, throw away the rest of the pack and start a new pack of pills that same day.
- You may not have your period this month, but this is expected. However, if you miss your period 2 months in a row, call your healthcare provider because you might be pregnant.
- You could become pregnant if you have sex during the first 7 days after you restart your pills. You should use a non-hormonal birth control method (such as a condom or spermicide) as a back-up if you have sex during the first 7 days after you restart your pills.

If you miss 1 or more peach pills in Week 4

- Throw away the missed pills.
- Keep taking 1 pill every day until you finish the pack.
- You do not need to use a non-hormonal back-up birth control method (such as condoms or spermicide).
- Make sure you start your next pack on time.

If you have any questions or are unsure about the information in this Instructions for Use, call your healthcare provider. You may also read the Patient Information.

Manufactured for: Exeltis USA, Inc., Florham Park, NJ 07932
Manufactured by: Laboratorios León Farma, S.A., León, Spain

This Instructions for Use has been approved by the U.S. Food and Drug Administration.

Revised Date: May 2020

PRINCIPAL DISPLAY PANEL - Carton

NDC 0642-7471-01

Tyblume™
(levonorgestrel and ethinyl estradiol) tablets,
0.1 mg/0.02 mg

CHEWABLE

Contains: 1 blister cards of 28 chewable tablets.
Each blister card contains 21 white tablets each containing 0.1 mg levonorgestrel

and 0.02 mg ethinyl estradiol, and 7 peach inert tablets. Contains lactose.

Rx only Oral use